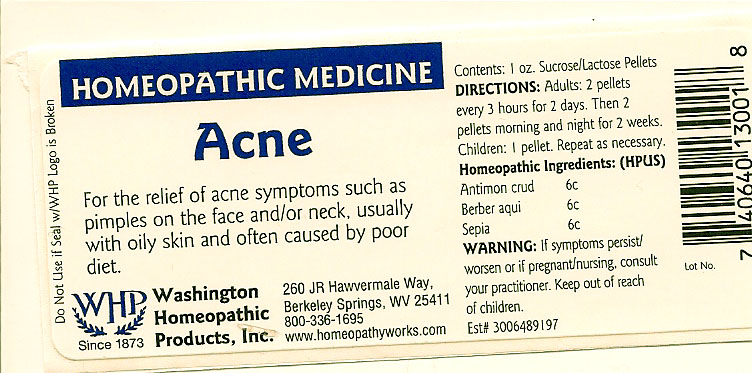 DRUG LABEL: Acne
NDC: 68428-017 | Form: PELLET
Manufacturer: Washington Homeopathic Products
Category: homeopathic | Type: HUMAN OTC DRUG LABEL
Date: 20191223

ACTIVE INGREDIENTS: ANTIMONY TRISULFIDE 6 [hp_C]/28 g; MAHONIA AQUIFOLIUM ROOT BARK 6 [hp_C]/28 g; SEPIA OFFICINALIS JUICE 6 [hp_C]/28 g
INACTIVE INGREDIENTS: SUCROSE; LACTOSE

DRUG FACTS

ACTIVE INGREDIENTS

ANTIMON CRUD 6C

BERBER AQUI 6C

SEPIA 6C

USES

To relieve the symptoms of acne symptoms such as pimples on the face and/or neck, usually with oily skin and often caused by poor diet.

KEEP OUT OF REACH OF CHILDREN

Keep this and all medicines out of reach of children.

INDICATIONS

ANTIMON CRUD Warts

BERBER AQUI Acne

SEPIA Indifference

STOP USE AND ASK DOCTOR

If symptoms persist/worsen or if pregnant/nursing, stop use and consult your practitioner.

DIRECTIONS

Adults 2 pellets every 3 hours for 2 days. Then 2 pellets morning and night for 2 weeks.

Children: 1 pellet. Repeat as necessary.

INACTIVE INGREDIENTS

Sucrose/Lactose

PRINCIPAL DISPLAY PANEL

Enter section text here